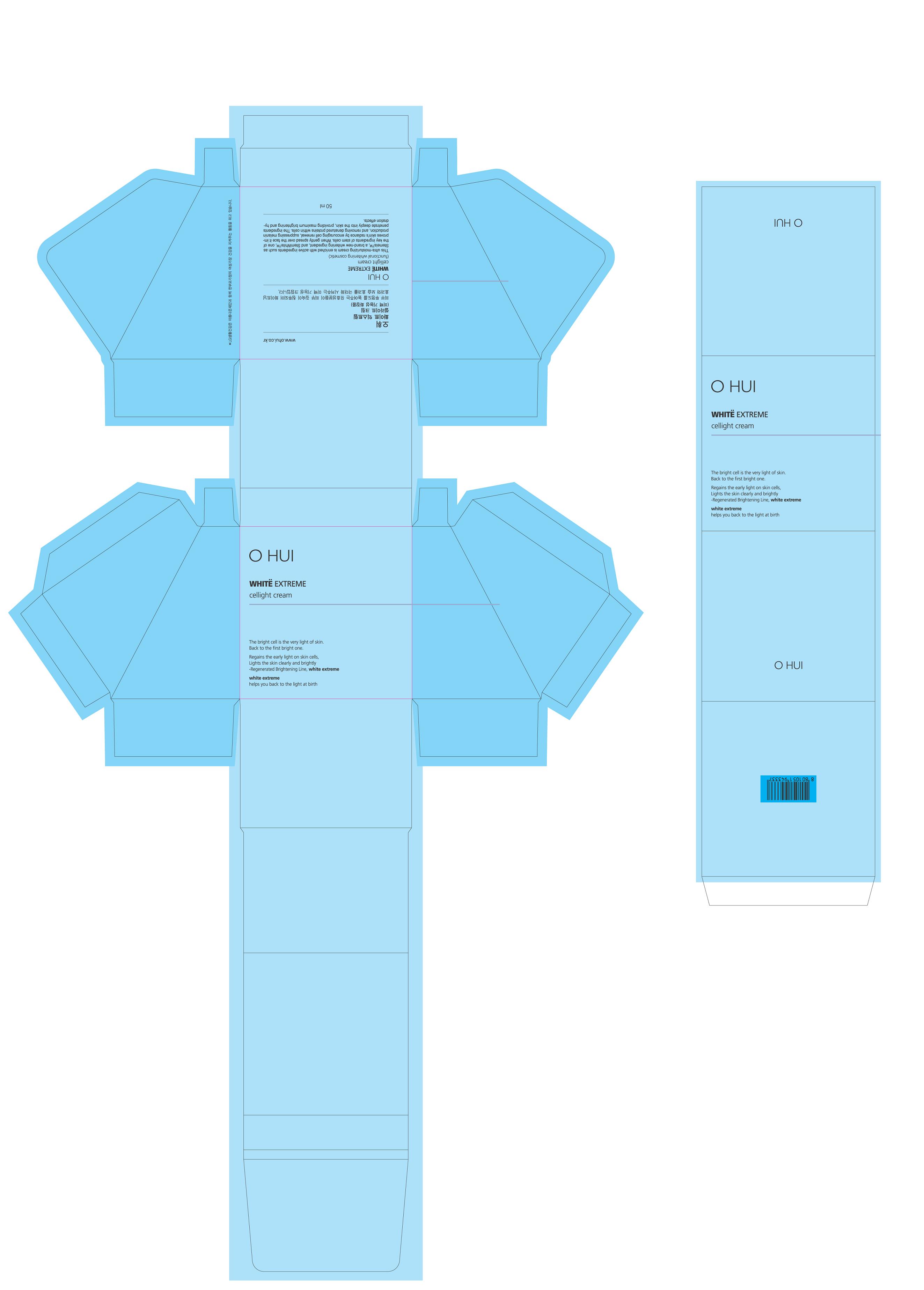 DRUG LABEL: O HUI WHITE EXTREME CELLIGHT
NDC: 53208-507 | Form: CREAM
Manufacturer: LG Household and Healthcare, Inc.
Category: otc | Type: HUMAN OTC DRUG LABEL
Date: 20120514

ACTIVE INGREDIENTS: PROTOCATECHUALDEHYDE 0.032 mL/100 mL
INACTIVE INGREDIENTS: WATER; GLYCERIN; DIPROPYLENE GLYCOL; TROLAMINE; MEDIUM-CHAIN TRIGLYCERIDES; CYCLOMETHICONE 5; GLYCERYL MONOSTEARATE; NEOPENTYL GLYCOL DICAPRATE; TREHALOSE; SQUALANE; 1,2-HEXANEDIOL; DIMETHICONE; PHENOXYETHANOL; ALPHA-TOCOPHEROL; COPPER; PANTHENOL; SODIUM METABISULFITE; ALCOHOL; EDETATE TRISODIUM

Drug Fact

ACTIVE INGREDIENT

PROTOCATECHUALDEHYDE 0.032%

PURPOSE

Whitening cream

Stop use if rash or irritation develops and lasts.

WHEN USING

Keep out of eyes. Rinse with water to remove.

INDICATIONS AND USAGE

Use to whiten skin.

Keep out of reach of children. Is swallowed, get medical help or contact a Poison Control Center right away.

INACTIVE INGREDIENT

WATER, DIPROPYLENE GLYCOL, CYCLOPENTASILOXANE, GLYCERIN, MEDIUM-CHAIN TRIGLYCERIDES, NEOPENTYL GLYCOL DICAPRATE, TREHALOSE, SQUALANE, 1,2-HEXANEDIOL, GLYCERYL STEARATE, DIMETHICONE, PANTHENOL, ALCOHOL, PHENOXYETHANOL, COPPER, ALPHA-TOCOPHEROL, EDETATE TRISODIUM, TROLAMINE, SODIUM METABISULFITE.

PACKAGE LABEL

OHUI
WHITE EXTREME

CELLIGHT CREAM

DOSAGE AND ADMINISTRATION

Use as needed to whiten skin.